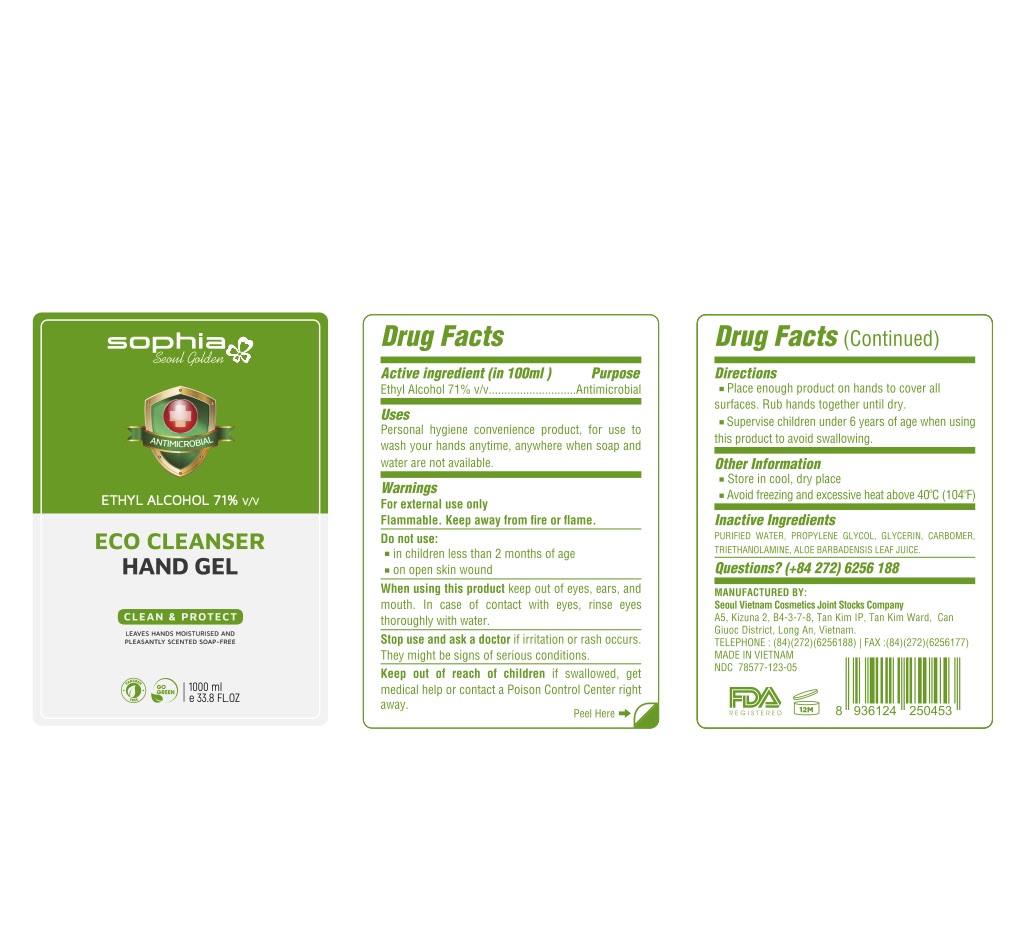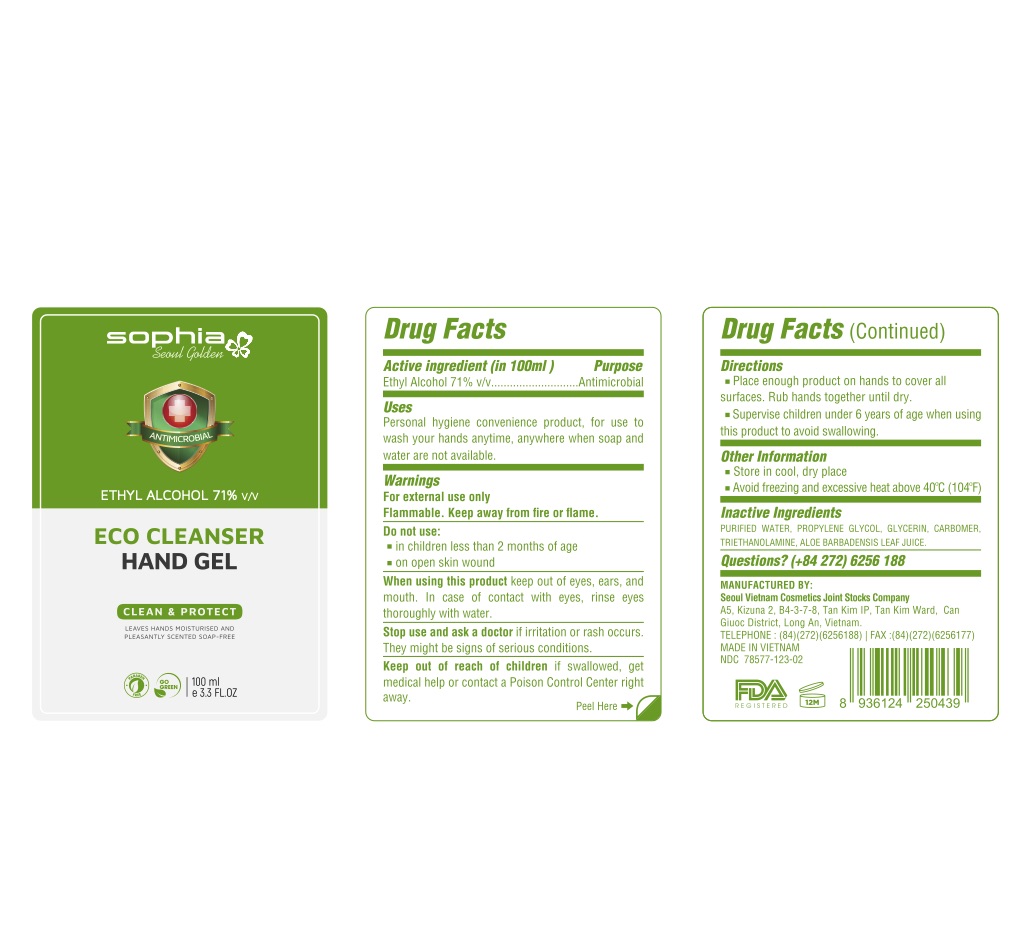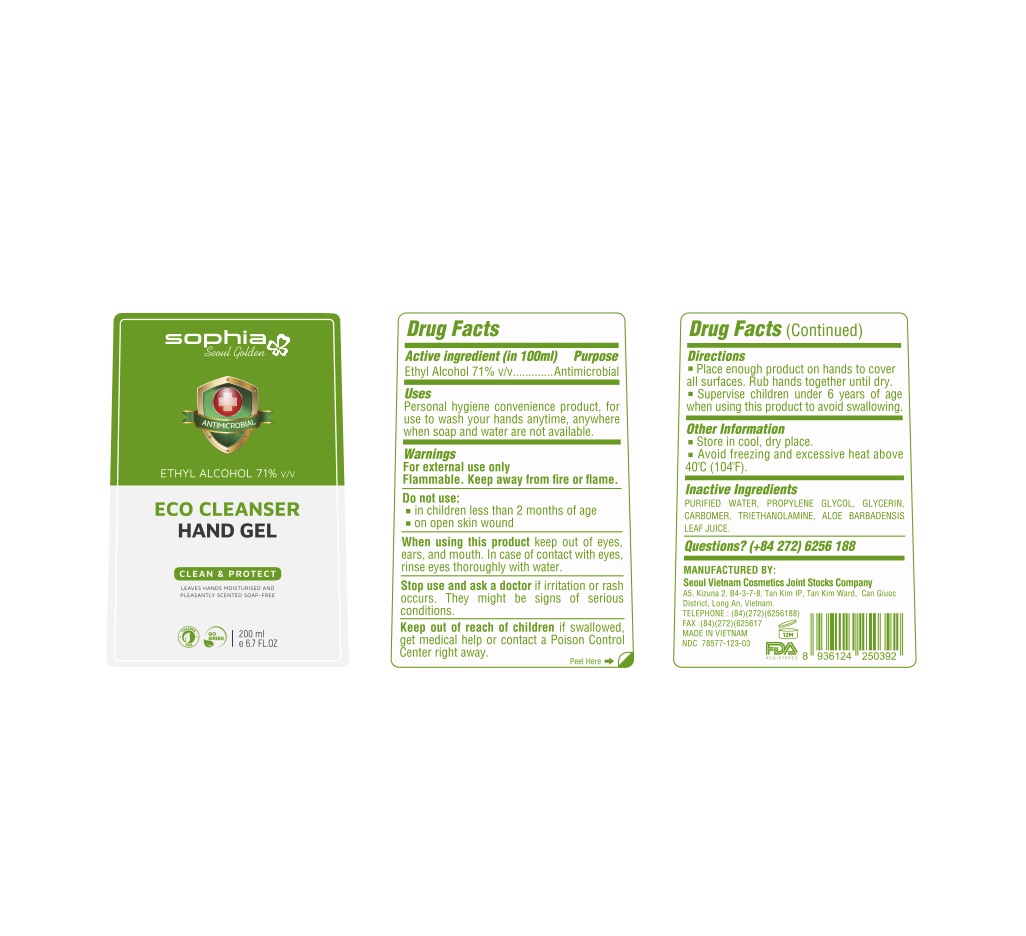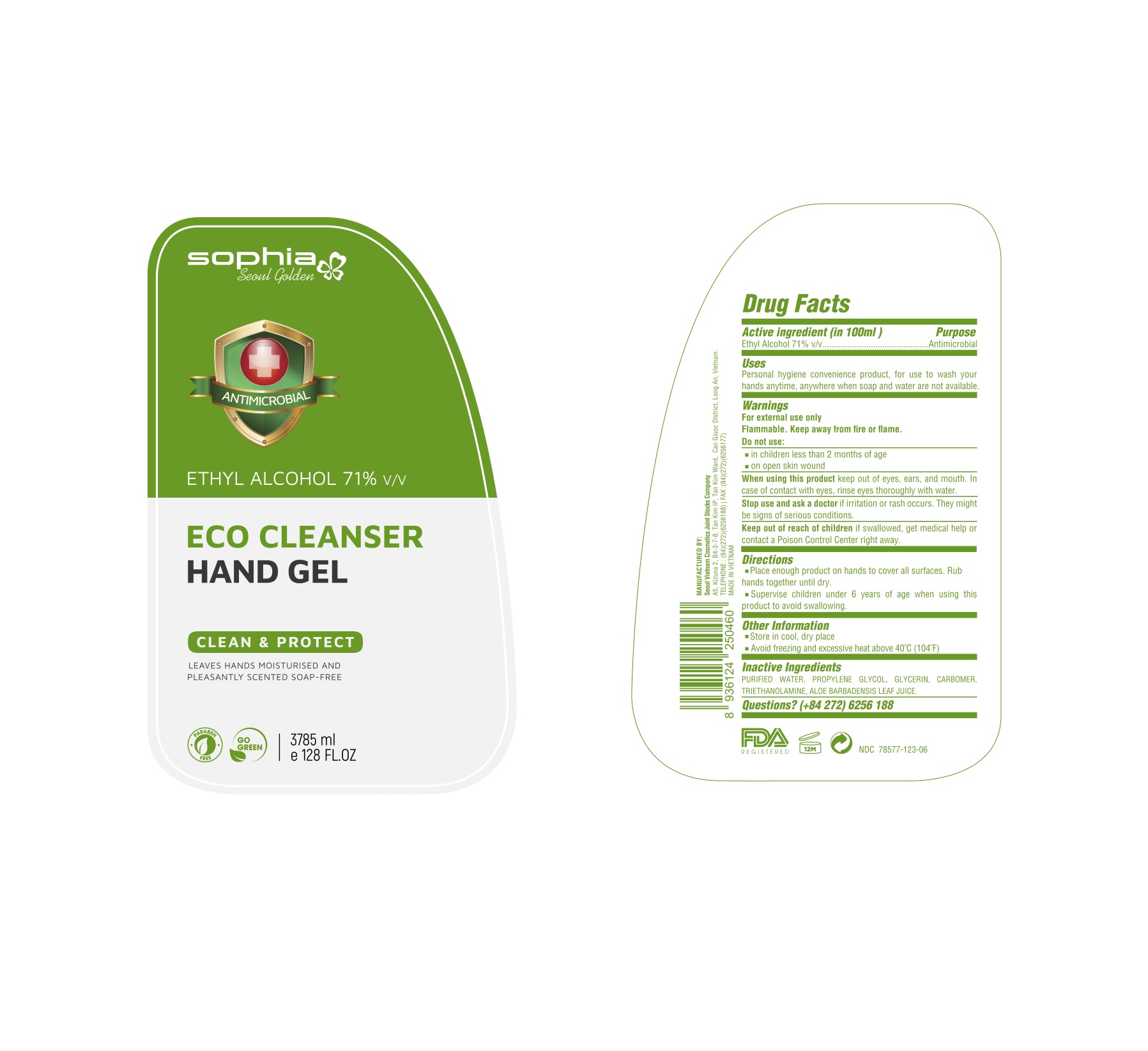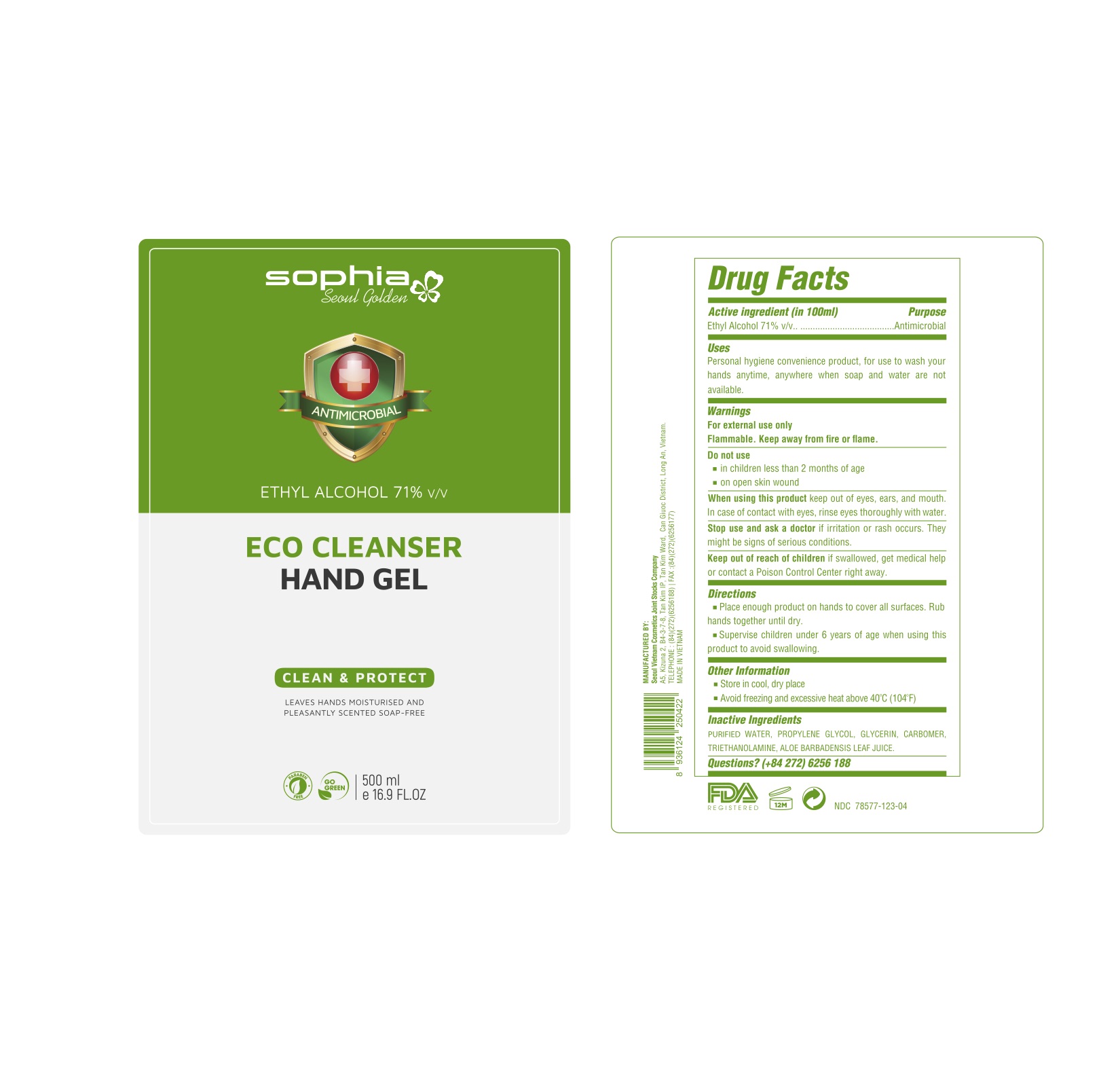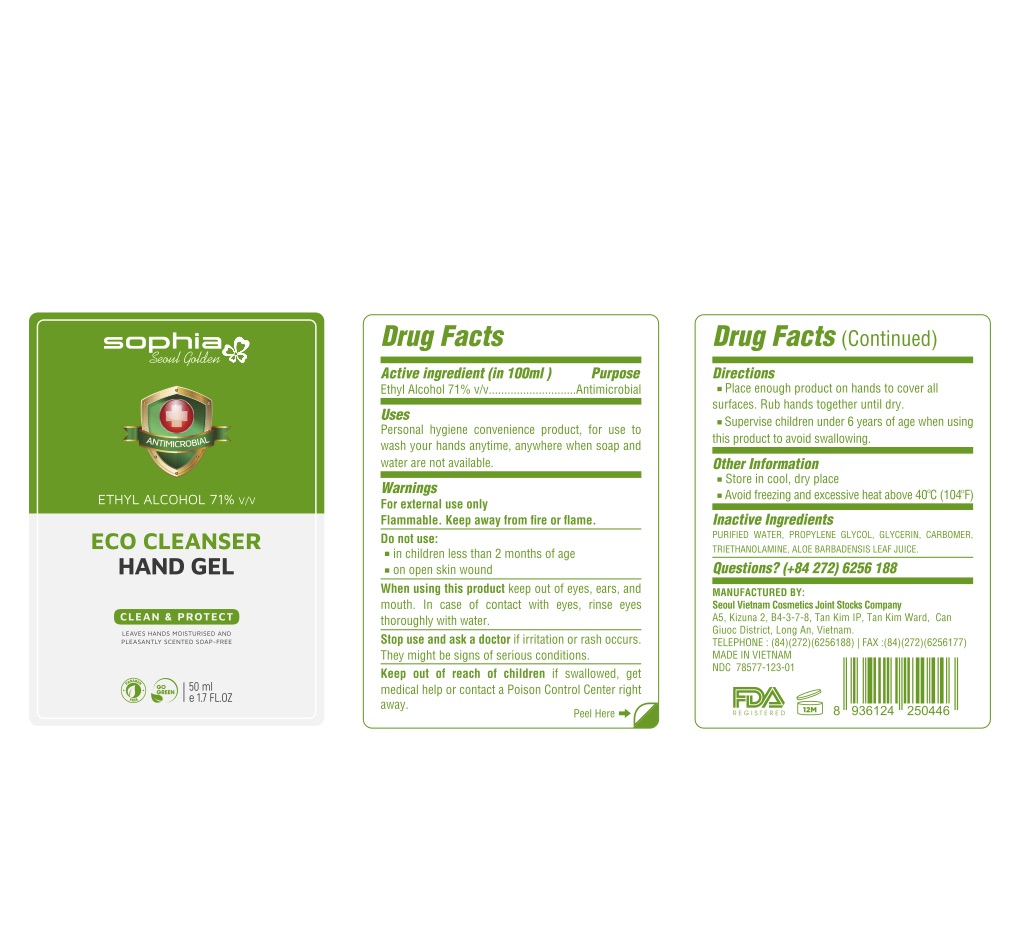 DRUG LABEL: Sophia Seoul Golden Eco Cleanser Hand Gel
NDC: 78577-123 | Form: GEL
Manufacturer: Seoul Vietnam Cosmetics Joint Stocks Company
Category: otc | Type: HUMAN OTC DRUG LABEL
Date: 20200617

ACTIVE INGREDIENTS: ALCOHOL 71 mL/100 mL
INACTIVE INGREDIENTS: GLYCERIN; WATER; ALOE VERA LEAF; TROLAMINE; PROPYLENE GLYCOL; CARBOMER HOMOPOLYMER, UNSPECIFIED TYPE

This is a hand sanitizer manufactured according to the Temporary Policy for Preparation of Certain Alcohol-Based Hand Sanitizer Products During the Public Health Emergency (CoViD-19); Guidance for Industry.

Active Ingredient(s)

Ethyl Alcohol 71% v/v. Purpose: Antimicrobial

Purpose

Antimicrobial

Use

Personal hygiene convenience product, for use to wash your hand anytime, anywhere when soap and water are not available.

Warnings

For external use only. Flammable. Keep away from heat or flame

Do not use

- in children less than 2 months of age
- on open skin wounds

When using this product keep out of eyes, ears, and mouth. In case of contact with eyes, rinse eyes thoroughly with water.
Stop use and ask a doctor if irritation or rash occurs. These may be signs of a serious condition.
Keep out of reach of children. If swallowed, get medical help or contact a Poison Control Center right away.

Stop use and ask a doctor if irritation or rash occurs. These may be signs of a serious condition.

Keep out of reach of children. If swallowed, get medical help or contact a Poison Control Center right away.

Directions

- Place enough product on hands to cover all surfaces. Rub hands together until dry.
- Supervise children under 6 years of age when using this product to avoid swallowing.

Other information

- Store in cool, dry place
- Avoid freezing and excessive heat above 40C (104F)

Inactive ingredients

Purified water, Propylene glycol, glycerin, carbomer, triethanolamine, aloe barbadensis leaft juice.

Uses

Personal hygiene convenience product, for use to wash your hands anytime, anywhere when soap and water are not available.

Package Label - Principal Display Panel

3785mL NDC: 78577-123-06

1000mL NDC: 78577-123-05

500mL NDC: 78577-123-04

200mL NDC: 78577-123-03

100mL NDC: 78577-123-02

50mL NDC: 78577-123-01